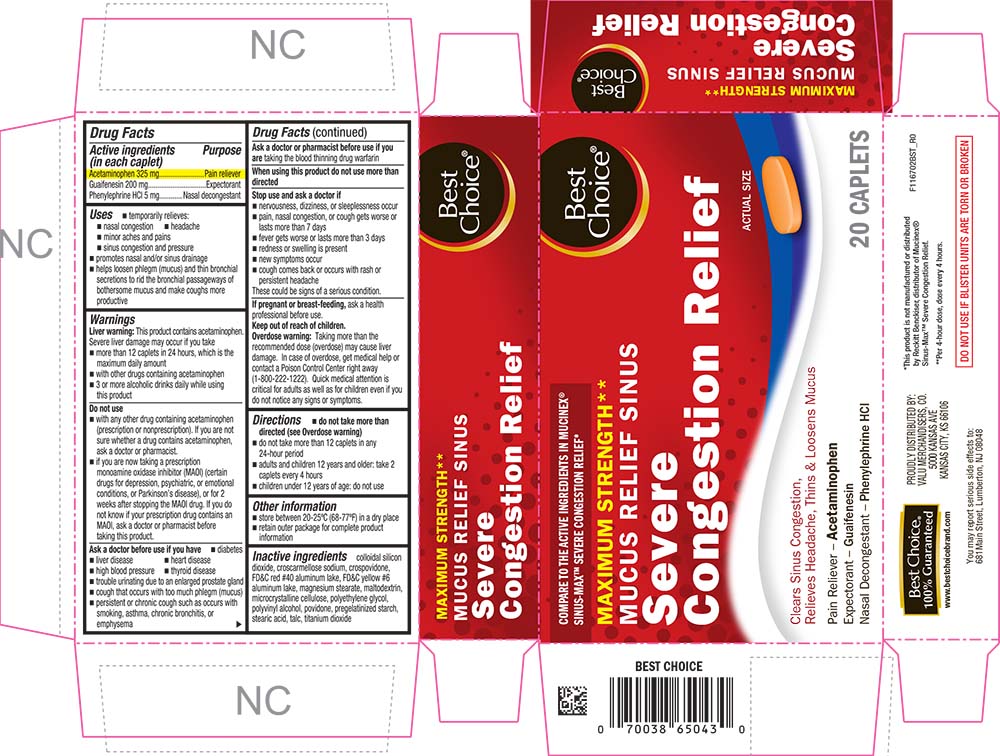 DRUG LABEL: Mucus Relief Sinus Severe Congestion Relief
NDC: 63941-167 | Form: TABLET, COATED
Manufacturer: VALU MERCHANDISERS COMPANY
Category: otc | Type: HUMAN OTC DRUG LABEL
Date: 20251211

ACTIVE INGREDIENTS: ACETAMINOPHEN 325 mg/1 1; GUAIFENESIN 200 mg/1 1; PHENYLEPHRINE HYDROCHLORIDE 5 mg/1 1
INACTIVE INGREDIENTS: SILICON DIOXIDE; CROSCARMELLOSE SODIUM; CROSPOVIDONE; FD&C RED NO. 40; FD&C YELLOW NO. 6; MAGNESIUM STEARATE; MALTODEXTRIN; CELLULOSE, MICROCRYSTALLINE; POLYETHYLENE GLYCOL, UNSPECIFIED; POLYVINYL ALCOHOL; POVIDONE; STARCH, CORN; STEARIC ACID; TALC; TITANIUM DIOXIDE

1167-BST-2021-1118

Drug Facts

ACTIVE INGREDIENT

Active ingredients (in each caplet) | Purpose
Acetaminophen 325 mg | Pain reliever
Guaifenesin 200 mg | Expectorant
Phenylephrine HCl 5 mg | Nasal decongestant

Uses

- temporarily relieves:
  - nasal congestion
  - headache
  - minor aches and pains
  - sinus congestion and pressure
- promotes nasal and/or sinus drainage
- helps loosen phlegm (mucus) and thin bronchial secretions to rid the bronchial passageways of bothersome mucus and make coughs more productive

Warnings

Liver warning

This product contains acetaminophen. Severe liver damage may occur if you take

- more than 12 caplets in 24 hours, which is the maximum daily amount
- with other drugs containing acetaminophen
- 3 or more alcoholic drinks daily while using this product

Do not use

- with any other drug containing acetaminophen (prescription or nonprescription). If you are not sure whether a drug contains acetaminophen, ask a doctor or pharmacist.
- if you are now taking a prescription monoamine oxidase inhibitor (MAOI) (certain drugs for depression, psychiatric, or emotional conditions, or Parkinson's disease), or for 2 weeks after stopping the MAOI drug. If you do not know if your prescription drug contains an MAOI, ask a doctor or pharmacist before taking this product.

Ask a doctor before use if you have

- liver disease
- heart disease
- diabetes
- high blood pressure
- thyroid disease
- trouble urinating due to an enlarged prostate gland
- persistent or chronic cough such as occurs with smoking, asthma, chronic bronchitis, or emphysema
- cough that occurs with too much phlegm (mucus)

Ask a doctor or pharmacist before use if you are taking the blood thinning drug warfarin

When using this product do not use more than directed

Stop use and ask a doctor if

- nervousness, dizziness, or sleeplessness occur
- pain, nasal congestion, or cough gets worse or lasts more than 7 days
- fever gets worse or lasts more than 3 days
- redness or swelling is present
- new symptoms occur
- cough comes back or occurs with rash or persistent headache

These could be signs of a serious condition.

PREGNANCY OR BREAST FEEDING

If pregnant or breast-feeding, ask a health professional before use.

Keep out of reach of children.

Overdose warning

Taking more than the recommended dose (overdose) may cause liver damage. In case of overdose, get medical help or contact a Poison Control Center right away (1-800-222-1222). Quick medical attention is critical for adults as well as for children even if you do not notice any signs or symptoms.

Directions

- do not take more than directed (see Overdose warning)
- do not take more than 12 caplets in any 24-hour period
- adults and children 12 years and older: take 2 caplets every 4 hours
- children under 12 years of age: do not use

Other information

- store between 20-25°C (68-77°F) in a dry place
- retain outer package for complete product information

Inactive ingredients

colloidal silicon dioxide, croscarmellose sodium, crospovidone, FD&C red #40 aluminum lake, FD&C yellow #6 aluminum lake, magnesium stearate, maltodextrin, microcrystalline cellulose, polyethylene glycol, polyvinyl alcohol, povidone, pregelatinized starch, stearic acid, talc, titanium dioxide

PRINCIPAL DISPLAY PANEL

COMPARE TO THE ACTIVE INGREDIENTS IN MUCINEX® SINUS-MAX® SEVERE CONGESTION RELIEF*

Best Choice®

MAXIUMUM STRENGTH**

MUCUS RELIEF SINUS

Severe Congestion Relief

Actual size

Clears Sinus Congestion, Relieves Headache, Thins & Loosens Mucus

Pain Reliever - Acetaminophen

Expectorant - Guaifenesin

Nasal Decongestant - Phenylephrine HCl

20 CAPLETS